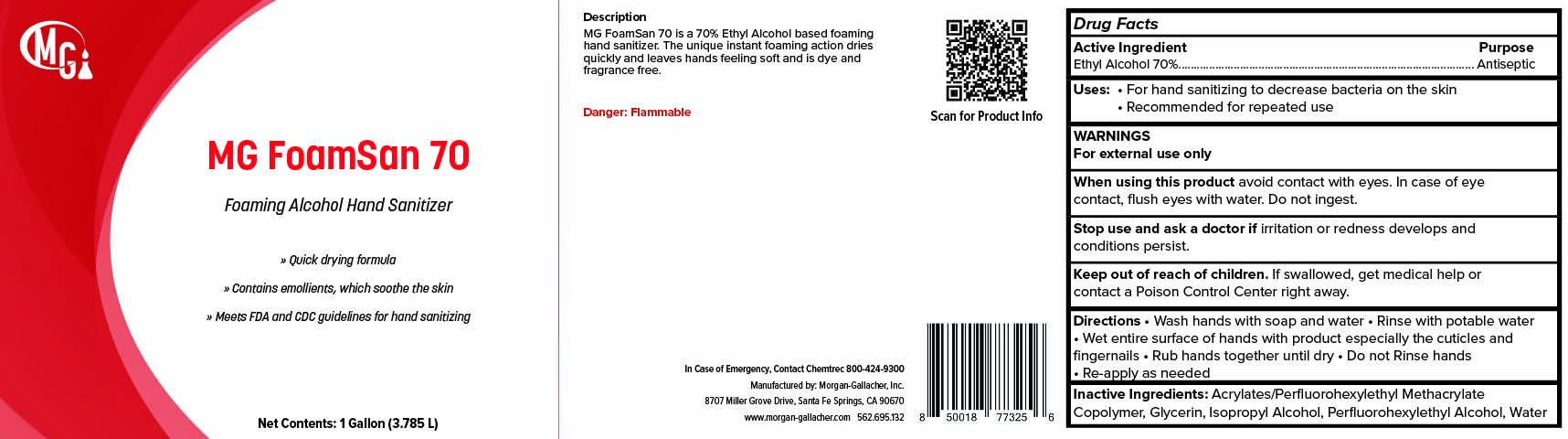 DRUG LABEL: MG FoamSan 70
NDC: 50241-223 | Form: LIQUID
Manufacturer: Morgan Gallacher Inc. DBA Custom Chemical Formulators Inc.
Category: otc | Type: HUMAN OTC DRUG LABEL
Date: 20251223

ACTIVE INGREDIENTS: ALCOHOL 0.7 L/1 L
INACTIVE INGREDIENTS: PEG-10 ACRYLATE/PERFLUOROHEXYLETHYL ACRYLATE COPOLYMER; GLYCERIN; ISOPROPYL ALCOHOL; 2-(PERFLUOROHEXYL)ETHANOL; WATER

MG FoamSan 70

ACTIVE INGREDIENT

Ethyl Alcohol ...........70.0% v/v

Purpose

Antiseptic

Uses

For hand sanitizing to decrease bacteria on the skin.

recommended for repeated use.

Warnings

For external use only.

When Using this Product

- Avoid contact with eyes.

- In case of eye contact, flush eyes with water.

Stop use and ask a doctor if

-Irritation or redness develops, if condition persists for more than 72 hours.

Keep out of reach of children. If swallowed, get medical help

or contact a Poison Control Center immediately.

Directions

-Pump a small amount of foam into palm of hand.

-Rub thoroughly over all surfaces of both hands.

-Rub hands together brisky until dry

-Use between hand washings to help reduce germ tranmission

Inactive Ingredients

Acrylates/Perfluorohexylethyl Methacrylate Copolymer, Glycerin, Isopropyl Alcohol, Perfluorohexylethyl Alcohol, Water.